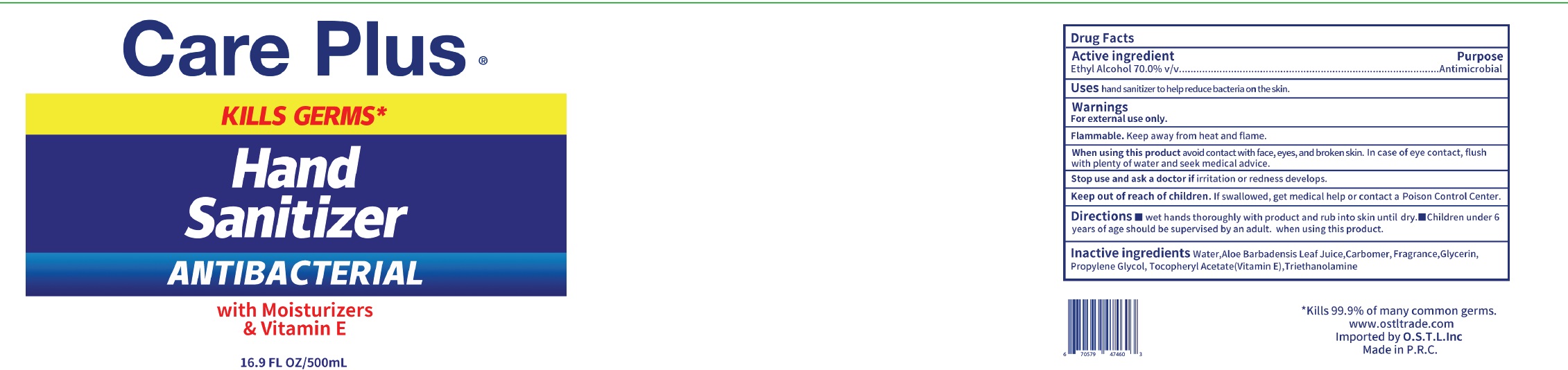 DRUG LABEL: Hand Sanitizer
NDC: 74746-003 | Form: GEL
Manufacturer: YUYAO WANGCHENG DAILY COMMODITY CO., LTD.
Category: otc | Type: HUMAN OTC DRUG LABEL
Date: 20200607

ACTIVE INGREDIENTS: ALCOHOL 70 mL/100 mL
INACTIVE INGREDIENTS: CARBOMER 934; WATER; PROPYLENE GLYCOL; TROLAMINE; ALOE VERA LEAF; .ALPHA.-TOCOPHEROL ACETATE; GLYCERIN

74746-003 hand sanitizer 70% Alcohol

Active Ingredient(s)

Isopropyl Alcohol 70% v/v.

Purpose

Antimicrobial

Use

hand sanitizer to help reduce bacteria on the skin.

Warnings

For external use only.
Flammable. Keep away from heat and flame.
When using this product avoid contact with face, eyes, and broken skin. In case of eye contact, flush
with plenty of water and seek medical advice.
Stop use and ask a doctor if irritation or redness develops.

Keep out of reach of children. If swallowed, get medical help or contact a Poison Control Center.

Directions

■wet hands thoroughly with product and rub into skin until dry. children under 6
years of age should be supervised by an adult. when using this product.

Inactive ingredients

Water,Aloe Barbadensis Leaf Juice,Carbomer, Fragrance,Glycerin,
Propylene Glycol, Tocopheryl Acetate(Vitamin E),Triethanolamine